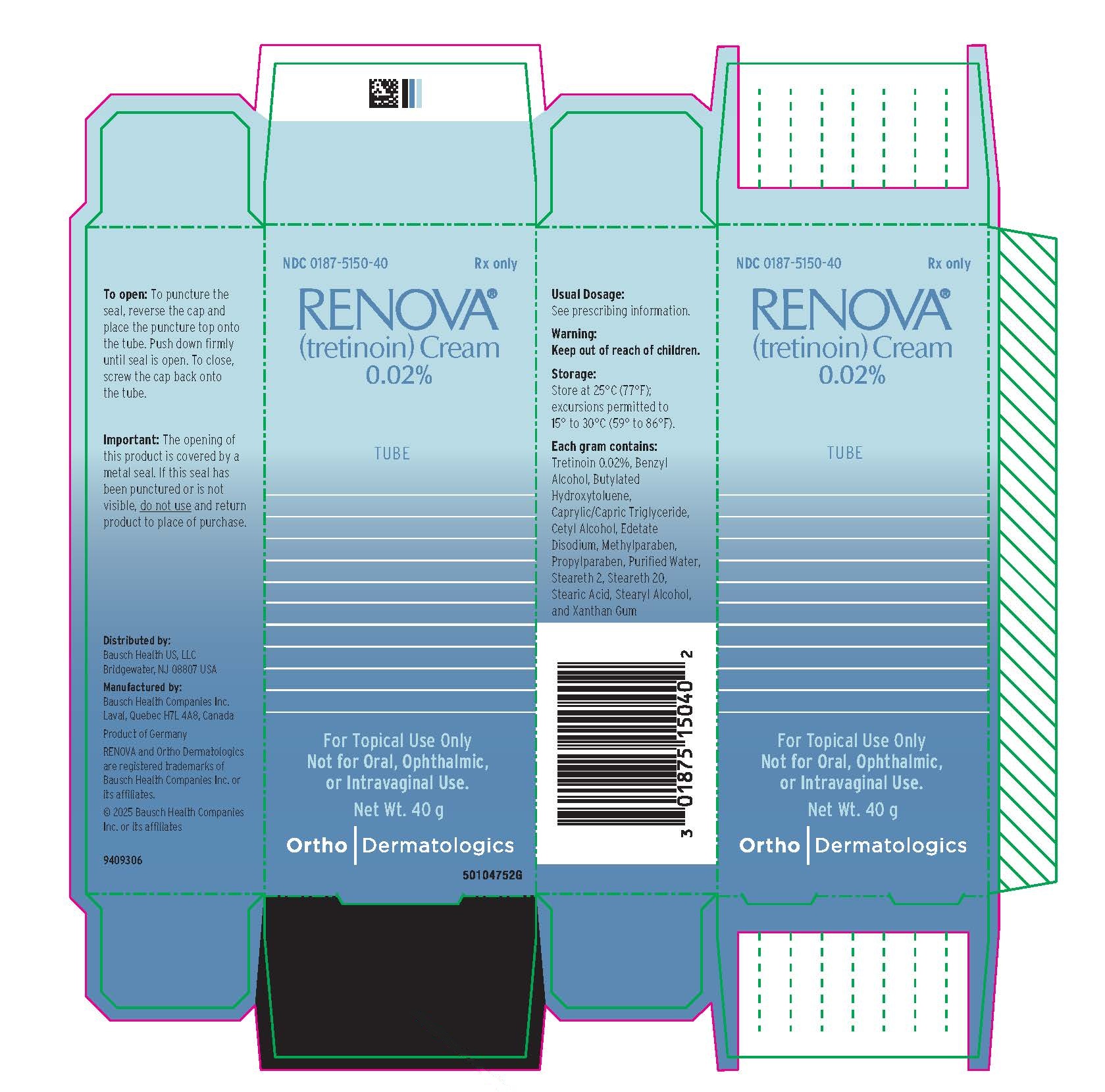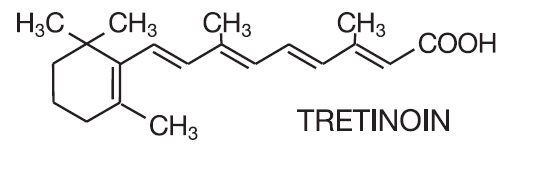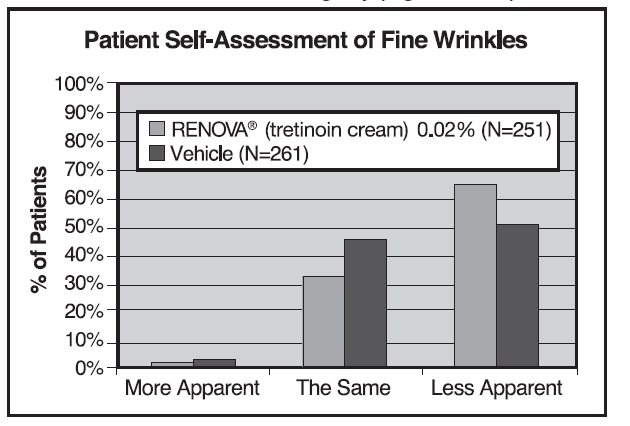 DRUG LABEL: Renova
NDC: 0187-5150 | Form: CREAM
Manufacturer: Bausch Health US LLC
Category: prescription | Type: HUMAN PRESCRIPTION DRUG LABEL
Date: 20260224

ACTIVE INGREDIENTS: TRETINOIN 0.2 mg/1 g
INACTIVE INGREDIENTS: BENZYL ALCOHOL; BUTYLATED HYDROXYTOLUENE; MEDIUM-CHAIN TRIGLYCERIDES; CETYL ALCOHOL; EDETATE DISODIUM; METHYLPARABEN; PROPYLPARABEN; WATER; STEARIC ACID; STEARYL ALCOHOL; STEARETH-2; STEARETH-20; XANTHAN GUM

RENOVA®
(tretinoin) Cream
0.02%

FOR TOPICAL USE ON THE FACE. NOT FOR ORAL, OPHTHALMIC, OR
INTRAVAGINAL USE.

DESCRIPTION

RENOVA® (tretinoin cream) 0.02% contains the active ingredient tretinoin in a cream base. Tretinoin is a yellow to light-orange crystalline powder having a characteristic floral odor. Tretinoin is soluble in dimethylsulfoxide, slightly soluble in polyethylene glycol 400, octanol, and 100% ethanol. It is practically insoluble in water and mineral oil, and it is insoluble in glycerin. The chemical name for tretinoin is (all-E)-3,7-dimethyl-9-(2,6,6-trimethyl-1-cyclohexen-1-yl)-2,4,6,8-nonatetraenoic acid. Tretinoin is also referred to as all-trans-retinoic acid and has a molecular weight of 300.44. The structural formula is represented below:

Tretinoin is available as RENOVA at a concentration of 0.02% w/w in an oil-in-water emulsion formulation consisting of benzyl alcohol, butylated hydroxytoluene, caprylic/capric triglyceride, cetyl alcohol, edetate disodium, methylparaben, propylparaben, purified water, stearic acid, stearyl alcohol, steareth 2, steareth 20, and xanthan gum.

CLINICAL PHARMACOLOGY

Tretinoin is an endogenous retinoid metabolite of Vitamin A that binds to intracellular receptors in the cytosol and nucleus, but cutaneous levels of tretinoin in excess of physiologic concentrations occur following application of a tretinoin-containing topical drug product. Although tretinoin activates three members of the retinoic acid (RAR) nuclear receptors (RARα, RARβ, and RARγ) which may act to modify gene expression, subsequent protein synthesis, and epithelial cell growth and differentiation, it has not been established whether the clinical effects of tretinoin are mediated through activation of retinoic acid receptors, other mechanisms such as irritation, or both.

The effect of tretinoin on skin with chronic photodamage has not been evaluated in animal studies. When hairless albino mice were treated topically with tretinoin shortly after a period of UVB irradiation, new collagen formation was demonstrated only in photodamaged skin. However, in human skin treated topically, adequate data have not been provided to demonstrate any increase in desmosine, hydroxyproline, or elastin mRNA. Application of 0.1% tretinoin cream to photodamaged human forearm skin was associated with an increase in antibody staining for procollagen I propeptide. No correlation was made between procollagen I propeptide staining with collagen I levels or with observed clinical effects. Thus, the relationships between the increased collagen in rodents, increased procollagen I propeptide in humans, and the clinical effects of tretinoin have not yet been clearly defined.

Tretinoin was shown to enhance UV-stimulated melanogenesis in pigmented mice. Generalized amyloid deposition in the basal layer of tretinoin-treated skin was noted in a 2-year mouse study. In a different study, hyalinization at tretinoin-treated skin sites was noted at doses beginning at 0.25 mg/kg in CD-1 mice.

The transdermal absorption of tretinoin from various topical formulations ranged from 1% to 31% of applied dose, depending on whether it was applied to healthy skin or dermatitic skin. No percutaneous absorption study was conducted with RENOVA (tretinoin cream) 0.02% in human volunteers. When percutaneous absorption of the oil-in-water emulsion formulation at 0.05% concentration was assessed in healthy male subjects with radiolabeled cream after a single application (n=7), as well as after repeated daily applications (n=7) for 28 days, the absorption of tretinoin was less than 2% and the extent of bioavailability was less after repeated application. No significant difference in endogenous concentrations of tretinoin was observed between single and repeated daily applications.

INDICATIONS AND USAGE

(To understand fully the indication for this product, please read the entire INDICATIONS AND USAGE section of the labeling.)

RENOVA (tretinoin cream) 0.02% is indicated as an adjunctive agent (see second bullet point below) for use in the mitigation (palliation) of fine facial wrinkles in patients who use comprehensive skin care and sunlight avoidance programs. RENOVA (tretinoin cream) 0.02% DOES NOT ELIMINATE WRINKLES, REPAIR SUN-DAMAGED SKIN, REVERSE PHOTOAGING, or RESTORE MORE YOUTHFUL or YOUNGER SKIN. In double-blind, vehicle-controlled clinical studies, many patients in the vehicle group achieved desired palliative effects on fine wrinkling of facial skin with the use of comprehensive skin care and sunlight avoidance programs including sunscreens, protective clothing, and non-prescription emollient creams.

- RENOVA (tretinoin cream) 0.02% has NOT DEMONSTRATED A MITIGATING EFFECT on significant signs of chronic sunlight exposure such as coarse or deep wrinkling, tactile roughness, mottled hyperpigmentation, lentigines, telangiectasia, skin laxity, keratinocytic atypia, melanocytic atypia, or dermal elastosis.
- RENOVA (tretinoin cream) 0.02% should be used under medical supervision as an adjunct to a comprehensive skin care and sunlight avoidance program that includes the use of effective sunscreens (minimum SPF of 15) and protective clothing.
- Patients with visible actinic keratosis and patients with a history of skin cancer were excluded from clinical trials of RENOVA (tretinoin cream) 0.02%. Thus the effectiveness and safety of RENOVA (tretinoin cream) 0.02% in these populations are not known at this time.
- Neither the safety nor the effectiveness of RENOVA (tretinoin cream) 0.02% for the prevention or treatment of actinic keratoses or skin neoplasms has been established.
- Neither the safety nor the efficacy of using RENOVA (tretinoin cream) 0.02% daily for greater than 52 weeks has been established, and daily use beyond 52 weeks has not been systematically and histologically investigated in adequate and well-controlled trials (see WARNINGS).

Clinical Trials

Four adequate and well-controlled multi-center trials and one single-center randomized, controlled trial were conducted involving a total of 324 evaluable patients treated with RENOVA (tretinoin cream) 0.02% and 332 evaluable patients treated with the vehicle cream on the face for 24 weeks with a comprehensive skin care and sun avoidance program, to assess the effects on fine and coarse wrinkling, mottled hyperpigmentation, tactile skin roughness, and laxity. Patients were evaluated at baseline on a 10-unit scale and changes from that baseline rating were categorized as follows:

Worsening: | Increase of 1 unit or more.
No improvement: | No change.
Minimal improvement: | Reduction of 1 unit.
Mild improvement: | Reduction of 2 units.
Moderate improvement: | Reduction of 3 units or more.

In these trials, the fine and coarse wrinkling, mottled hyperpigmentation, tactile roughness, and laxity of the facial skin were thought to be caused by multiple factors which included intrinsic aging or environmental factors, such as chronic sunlight exposure.

Two of the five trials provided adequate demonstration of efficacy for mitigation of fine facial wrinkling. No two of the five trials adequately demonstrated efficacy for mitigation of coarse wrinkling, mottled hyperpigmentation, tactile skin roughness, and laxity. Data for fine wrinkling (the indication for which RENOVA (tretinoin cream) 0.02% demonstrated efficacy) from all five trials (four studies in lightly pigmented subjects with Fitzpatrick Skin Types I-III and one study in darkly pigmented subjects with Fitzpatrick Skin Types IV-VI) is provided below:

FINE WRINKLING IN LIGHTLY PIGMENTED SUBJECTS
 | Subjects Using RENOVA (tretinoin cream) 0.02% + CSP* (N=279) | Vehicle + CSP* (N=280)
Worsened | 1% | 3%
No Change | 40% | 58%
Minimal Improvement | 35% | 27%
Mild Improvement | 15% | 9%
Moderate Improvement | 10% | 3%
A single-center study (N=107) in darkly pigmented, mostly African-American, subjects with Fitzpatrick Skin Types IV-VI demonstrated minimal or mild improvement in fine facial wrinkling in 43% of patients using Vehicle + CSP* compared to 29% of subjects using RENOVA (tretinoin cream) 0.02% + CSP*. Although fewer darkly pigmented subjects improved with RENOVA (tretinoin cream) 0.02% than with vehicle, these findings may reflect the small size of this study.
* CSP = Comprehensive skin protection and sunlight avoidance programs including use of sunscreens, protective clothing, and non-prescription emollient creams.

Self-assessment of fine wrinkles after 24 weeks of treatment with either RENOVA (tretinoin cream) 0.02% or Vehicle from the four studies in lightly pigmented patients showed the following:

No studies have been conducted comparing the facial irritation or efficacy of RENOVA (tretinoin cream) 0.02% to RENOVA (tretinoin cream) 0.05% (older marketed formulation).

Patients may lose some of the mitigating effects of RENOVA (tretinoin cream) 0.02% after 12 weeks of discontinuation of RENOVA (tretinoin cream) 0.02% from their comprehensive skin care and sunlight avoidance program.

CONTRAINDICATIONS

This drug is contraindicated in individuals with a history of sensitivity reactions to any of its components. It should be discontinued if hypersensitivity to any of its ingredients is noted.

WARNINGS

- RENOVA (tretinoin cream) 0.02% is a dermal irritant, and the results of continued irritation of the skin for greater than 52 weeks in chronic use with RENOVA (tretinoin cream) 0.02% are not known. There is evidence of atypical changes in melanocytes and keratinocytes and of increased dermal elastosis in some patients treated with RENOVA (tretinoin cream) 0.05% for longer than 48 weeks. The significance of these findings and their relevance for RENOVA (tretinoin cream) 0.02% are unknown.
- RENOVA (tretinoin cream) 0.02% should not be administered if the patient is also taking drugs known to be photosensitizers (e.g., thiazides, tetracyclines, fluoroquinolones, phenothiazines, sulfonamides) because of the possibility of augmented phototoxicity.

Exposure to sunlight (including sunlamps) should be avoided or minimized during use of RENOVA (tretinoin cream) 0.02% because of heightened sunburn susceptibility. Patients should be warned to use sunscreens (minimum SPF of 15) and protective clothing when using RENOVA (tretinoin cream) 0.02%. Patients with sunburn should be advised not to use RENOVA (tretinoin cream) 0.02% until fully recovered. Patients who may have considerable sun exposure, e.g., due to their occupation, and those patients with inherent sensitivity to sunlight should exercise caution when using RENOVA (tretinoin cream) 0.02% and follow the precautions outlined in the Patient Package Insert.

RENOVA (tretinoin cream) 0.02% should be kept out of the eyes, mouth, angles of the nose, and mucous membranes. Topical use may cause severe local erythema, pruritus, burning, stinging, and peeling at the site of application. If the degree of local irritation warrants, patients should be directed to use less medication, decrease the frequency of application, discontinue use temporarily, or discontinue use altogether and consider additional appropriate therapy.

Tretinoin has been reported to cause severe irritation on eczematous skin and should be used only with caution in patients with this condition.

Application of larger amounts of medication than recommended has not been shown to lead to more rapid or better results, and marked redness, peeling, or discomfort may occur.

PRECAUTIONS

General:

RENOVA (tretinoin cream) 0.02% should be used only as an adjunct to a comprehensive skin care and sunlight avoidance program (see INDICATIONS AND USAGE).

If a drug sensitivity, chemical irritation, or a systemic adverse reaction develops, use of RENOVA (tretinoin cream) 0.02% should be discontinued. Weather extremes, such as wind or cold, may be more irritating to patients using tretinoin-containing products.

Information for Patients:

RENOVA (tretinoin cream) 0.02% is to be used as described below unless otherwise directed by your physician:

1. It is for use on the face.
2. Avoid contact with the eyes, ears, nostrils, angles of the nose, and mouth. RENOVA (tretinoin cream) 0.02% may cause severe redness, itching, burning, stinging, and peeling if used on these areas.
3. In the evening, gently wash your face with a mild soap. Pat skin dry and wait 20 to 30 minutes before applying RENOVA (tretinoin cream) 0.02%. Apply only a small pearl-sized (about ¼ inch or 5 mm diameter) amount of RENOVA (tretinoin cream) 0.02% to your face at one time. This should be enough to cover the entire affected area lightly.
4. Do not wash your face for at least 1 hour after applying RENOVA (tretinoin cream) 0.02%.
5. For best results, you are advised not to apply another skin care product or cosmetic for at least 1 hour after applying RENOVA (tretinoin cream) 0.02%.
6. In the morning, apply a moisturizing sunscreen, SPF 15 or greater.
7. RENOVA (tretinoin cream) 0.02% is a serious medication. Do not use RENOVA (tretinoin cream) 0.02% if you are pregnant or attempting to become pregnant. If you become pregnant while using RENOVA (tretinoin cream) 0.02%, please contact your physician immediately.
8. Avoid sunlight and other medicines that may increase your sensitivity to sunlight.
9. RENOVA (tretinoin cream) 0.02% does not remove wrinkles or repair sun-damaged skin.

Please refer to the Patient Package Insert for additional patient information.

Drug Interactions:

Concomitant topical medications, medicated or abrasive soaps, shampoos, cleansers, cosmetics with a strong drying effect, products with high concentrations of alcohol, astringents, spices or lime, permanent wave solutions, electrolysis, hair depilatories or waxes, and products that may irritate the skin should be used with caution in patients being treated with RENOVA (tretinoin cream) 0.02% because they may increase irritation with RENOVA (tretinoin cream) 0.02%.

RENOVA (tretinoin cream) 0.02% should not be administered if the patient is also taking drugs known to be photosensitizers (e.g., thiazides, tetracyclines, fluoroquinolones, phenothiazines, sulfonamides) because of the possibility of augmented phototoxicity.

Carcinogenesis, Mutagenesis, Impairment of Fertility:

In a 91-week dermal study in which CD-1 mice were administered 0.017% and 0.035% formulations of tretinoin, cutaneous squamous cell carcinomas and papillomas in the treatment area were observed in some female mice. These concentrations are near the tretinoin concentration of this clinical formulation (0.02%). A dose-related incidence of liver tumors in male mice was observed at those same doses. The maximum systemic doses associated with the 0.017% and 0.035% formulations are 0.5 and 1.0 mg/kg/day. These doses are 10 and 20 times the maximum human systemic dose, when adjusted for total body surface area. The biological significance of these findings is not clear because they occurred at doses that exceeded the dermal maximally tolerated dose (MTD) of tretinoin and because they were within the background natural occurrence rate for these tumors in this strain of mice. There was no evidence of carcinogenic potential when 0.025 mg/kg/day of tretinoin was administered topically to mice (0.5 times the maximum human systemic dose, adjusted for total body surface area). For purposes of comparisons of the animal exposure to systemic human exposure, the maximum human systemic dose is defined as 1 gram of RENOVA (tretinoin cream) 0.02% applied daily to a 50 kg person (0.004 mg tretinoin/kg body weight).

Studies in hairless albino mice suggest that concurrent exposure to tretinoin may enhance the tumorigenic potential of carcinogenic doses of UVB and UVA light from a solar simulator. This effect has been confirmed in a later study in pigmented mice, and dark pigmentation did not overcome the enhancement of photocarcinogenesis by 0.05% tretinoin. Although the significance of these studies to humans is not clear, patients should minimize exposure to sunlight or artificial ultraviolet irradiation sources.

The mutagenic potential of tretinoin was evaluated in the Ames assay and in the in vivo mouse micronucleus assay, both of which were negative.

In dermal Segment I fertility studies in rats, slight (not statistically significant) decreases in sperm count and motility were seen at 0.5 mg/kg/day (20 times the maximum human systemic dose adjusted for total body surface area), and slight (not statistically significant) increases in the number and percent of nonviable embryos in females treated with 0.25 mg/kg/day (10 times the maximum human systemic dose adjusted for total body surface area) and above were observed. A dermal Segment III study with RENOVA (tretinoin cream) 0.02% has not been performed in any species. In oral Segment I and Segment III studies in rats with tretinoin, decreased survival of neonates and growth retardation were observed at doses in excess of 2 mg/kg/day (83 times the human topical dose adjusted for total body surface area).

Pregnancy:

Teratogenic Effects

ORAL tretinoin has been shown to be teratogenic in rats, mice, rabbits, hamsters, and subhuman primates. It was teratogenic and fetotoxic in Wistar rats when given orally or topically in doses greater than 1 mg/kg/day (42 times the maximum human systemic dose normalized for total body surface area). However, variations in teratogenic doses among various strains of rats have been reported. In the cynomolgus monkey, which, metabolically, is closer to humans for tretinoin than the other species examined, fetal malformations were reported at doses of 10 mg/kg/day or greater, but none were observed at 5 mg/kg/day (417 times the maximum human systemic dose adjusted for total body surface area), although increased skeletal variations were observed at all doses. A dose-related increase in embryolethality and abortion was reported. Similar results have also been reported in pigtail macaques.

TOPICAL tretinoin in animal teratogenicity tests has generated equivocal results. There is evidence for teratogenicity (shortened or kinked tail) of topical tretinoin in Wistar rats at doses greater than 1 mg/kg/day (42 times the maximum human systemic dose adjusted for total body surface area). Anomalies (humerus: short 13%, bent 6%, os parietal incompletely ossified 14%) have also been reported when 10 mg/kg/day was dermally applied.

There are other reports in New Zealand White rabbits administered doses of greater than 0.2 mg/kg/day (17 times the maximum human systemic dose adjusted for total body surface area) of an increased incidence of domed head and hydrocephaly, typical of retinoid-induced fetal malformations in this species.

In contrast, several well-controlled animal studies have shown that dermally applied tretinoin may be fetotoxic, but not overtly teratogenic, in rats and rabbits at doses of 1.0 and 0.5 mg/kg/day, respectively (42 times the maximum human systemic dose adjusted for total body surface area in both species).

With widespread use of any drug, a small number of birth defect reports associated temporally with the administration of the drug would be expected by chance alone. Thirty human cases of temporally associated congenital malformations have been reported during two decades of clinical use of another formulation of topical tretinoin (Retin-A®). Although no definite pattern of teratogenicity and no causal association has been established from these cases, five of the reports describe the rare birth defect category holoprosencephaly (defects associated with incomplete midline development of the forebrain). The significance of these spontaneous reports in terms of risk to the fetus is not known.

Non-teratogenic Effects

Dermal tretinoin has been shown to be fetotoxic in rabbits when administered 0.5 mg/kg/day (42 times the maximum human systemic dose normalized for total body surface area). Oral tretinoin has been shown to be fetotoxic, resulting in skeletal variations and increased intrauterine death, in rats when administered 2.5 mg/kg/day (104 times the maximum human systemic dose adjusted for total body surface area).

There are, however, no adequate and well-controlled studies in pregnant women. RENOVA (tretinoin cream) 0.02% should not be used during pregnancy.

Nursing Mothers:

It is not known whether this drug is excreted in human milk. Since many drugs are excreted in human milk, mitigation of fine facial wrinkles with RENOVA (tretinoin cream) 0.02% may be postponed in nursing mothers until after completion of the nursing period.

Pediatric Use:

Safety and effectiveness in patients less than 18 years of age have not been established.

Geriatric Use:

In clinical studies with RENOVA (tretinoin cream) 0.02%, patients aged 65 to 71 did not demonstrate a significant difference for improvement in fine wrinkling when compared to patients under the age of 65. Patients aged 65 and over may demonstrate slightly more irritation, although the differences were not statistically significant in the clinical studies for RENOVA (tretinoin cream) 0.02%. Safety and effectiveness of RENOVA (tretinoin cream) 0.02% in individuals older than 71 years of age have not been established.

ADVERSE REACTIONS

(See WARNINGS and PRECAUTIONS.)

In double-blind, vehicle-controlled studies involving 339 patients who applied RENOVA (tretinoin cream) 0.02% to their faces, adverse reactions associated with the use of RENOVA (tretinoin cream) 0.02% were limited primarily to the skin. Almost all patients reported one or more local reactions such as peeling, dry skin, burning, stinging, erythema, and pruritus. In 32% of all study patients, skin irritation was reported that was severe, led to temporary discontinuation of RENOVA (tretinoin cream) 0.02%, or led to use of a mild topical corticosteroid. About 7% of patients using RENOVA (tretinoin cream) 0.02%, compared to less than 1% of the control patients, had sufficiently severe local irritation to warrant short-term use of mild topical corticosteroids to alleviate local irritation. About 4% of patients had to discontinue use of RENOVA (tretinoin cream) 0.02% because of adverse reactions.

Approximately 2% of spontaneous postmarketing adverse event reporting for RENOVA (tretinoin cream) 0.05% were for skin hypo- or hyperpigmentation. Other spontaneously reported adverse events for RENOVA (tretinoin cream) 0.05% predominantly appear to be local reactions similar to those seen in clinical trials.

To report SUSPECTED ADVERSE REACTIONS, contact Bausch Health US, LLC at 1-800-321-4576 or FDA at 1-800-FDA-1088 or www.fda.gov/medwatch.

OVERDOSAGE

Application of larger amounts of medication than recommended has not been shown to lead to more rapid or better results, and marked redness, peeling, or discomfort may occur. Oral ingestion of the drug may lead to the same side effects as those associated with excessive oral intake of Vitamin A.

DOSAGE AND ADMINISTRATION

- Do NOT use RENOVA (tretinoin cream) 0.02% if the patient is pregnant or is attempting to become pregnant or is at high risk of pregnancy.
- Do NOT use RENOVA (tretinoin cream) 0.02% if the patient is sunburned or if the patient has eczema or other chronic skin conditions of the face.
- Do NOT use RENOVA (tretinoin cream) 0.02% if the patient is inherently sensitive to sunlight.
- Do NOT use RENOVA (tretinoin cream) 0.02% if the patient is also taking drug(s) known to be photosensitizers (e.g., thiazides, tetracyclines, fluoroquinolones, phenothiazines, sulfonamides) because of the possibility of augmented phototoxicity.

Patients require detailed instruction to obtain maximal benefits and to understand all the precautions necessary to use this product with greatest safety. The physician should review the Patient Package Insert.

RENOVA (tretinoin cream) 0.02% should be applied to the face once a day in the evening, using only enough to cover the entire affected area lightly. Patients should gently wash their faces with a mild soap, pat the skin dry, and wait 20 to 30 minutes before applying RENOVA (tretinoin cream) 0.02%. The patient should apply a small pearl-sized (about ¼ inch or 5 mm diameter) amount of cream to cover the entire affected area lightly. Caution should be taken when applying the cream to avoid the eyes, ears, nostrils, and mouth.

Application of RENOVA (tretinoin cream) 0.02% may cause a transitory feeling of warmth or slight stinging.

Mitigation (palliation) of fine facial wrinkling may occur gradually over the course of therapy. Up to 6 months of therapy may be required before the effects are seen.

With discontinuation of RENOVA (tretinoin cream) 0.02% therapy, some patients may lose the mitigating effects of RENOVA (tretinoin cream) 0.02% on fine facial wrinkles. The safety and effectiveness of using RENOVA (tretinoin cream) 0.02% daily for greater than 52 weeks have not been established.

Application of larger amounts of medication than recommended may not lead to more rapid or better results, and marked redness, peeling, or discomfort may occur.

Patients treated with RENOVA (tretinoin cream) 0.02% may use cosmetics but the areas to be treated should be cleansed before the medication is applied (see PRECAUTIONS).

HOW SUPPLIED

RENOVA® (tretinoin cream), 0.02% is supplied in
20 g tube (NDC 0187-5150-20),
40 g tube (NDC 0187-5150-40),
60 g tube (NDC 0187-5150-60),
44 g pump (NDC 0187-5150-44).

Storage:

Store at 25°C (77°F); excursions permitted to 15° to 30°C (59° to 86°F).

QUESTIONS:

Physicians and Pharmacists can call 1-800-321-4576, from 8:30 a.m. to 4:30 p.m. Eastern Time, Monday through Friday.

Distributed by:
Bausch Health US, LLC
Bridgewater, NJ 08807 USA

Manufactured by:
Bausch Health Companies Inc.
Laval, Quebec H7L 4A8, Canada

RENOVA and Retin-A are registered trademarks of Bausch Health Companies Inc. or its affiliates.

© 2025 Bausch Health Companies Inc. or its affiliates

Rev. 11/2025 9418704

PATIENT INFORMATION
RENOVA®
(tretinoin) Cream
0.02%
RENOVA (reh-NO-vah)
Generic Name: Tretinoin Cream (0.02%)
Use only on the Face

Read this leaflet carefully before you start to use your medicine. Read the information you get every time you get more medicine. There may be new information about the drug. This leaflet does not take the place of talks with your doctor. It is important for you to talk with your doctor about how to use RENOVA® (tretinoin cream) 0.02% for the best results and how to reduce side effects.

What is the Most Important Information about RENOVA (tretinoin cream) 0.02%?

RENOVA (tretinoin cream) 0.02% is a serious medicine. Do not use RENOVA (tretinoin cream) 0.02% if you are pregnant or attempting to become pregnant. If you become pregnant while using RENOVA (tretinoin cream) 0.02%, please contact your doctor immediately.

Avoid sunlight and other medicines that may increase your sensitivity to sunlight (see “Who should not use RENOVA (tretinoin cream) 0.02%?”).

RENOVA (tretinoin cream) 0.02% does not remove wrinkles or repair sun-damaged skin. (see “What is RENOVA (tretinoin cream) 0.02%?” for more details.)

What is RENOVA (tretinoin cream) 0.02%?

RENOVA (tretinoin cream) 0.02% is a prescription medicine that may reduce fine facial wrinkles. It is for patients who are using a total skin care and sunlight avoidance program. RENOVA (tretinoin cream) 0.02% does not remove wrinkles or repair sun-damaged skin. RENOVA (tretinoin cream) 0.02% does not work for everyone who uses it. It may work better for some patients than for others. RENOVA (tretinoin cream) 0.02% should be used only under the guidance of your doctor as part of a sunlight avoidance and total skin care program. This program should include avoiding sunlight as much as possible, using clothing to protect you from sunlight, using sunscreens with a minimum SPF of 15, and using face creams that add moisture to the skin.

When you use RENOVA (tretinoin cream) 0.02%, you will not see improvement right away. Generally, you may notice some effects in 3 to 4 months. If RENOVA (tretinoin cream) 0.02% treatment is stopped, the improvement may gradually disappear.

The use of RENOVA (tretinoin cream) 0.02% in patients for more than 52 weeks has not been studied. Therefore, it is not known if RENOVA (tretinoin cream) 0.02% is safe or works if used longer than 52 weeks. In a study in people with medium to dark skin color, RENOVA (tretinoin cream) 0.02% has not demonstrated a benefit over a sunlight avoidance and total skin care program. RENOVA (tretinoin cream) 0.02% has not been studied in people with visible actinic keratoses or in people with a history of skin cancer.

Who should not use RENOVA (tretinoin cream) 0.02%?

Do not use RENOVA (tretinoin cream) 0.02% if:

- you are pregnant or plan to become pregnant. If you become pregnant while using RENOVA (tretinoin cream) 0.02%, please contact your doctor immediately.
- you are sunburned or your skin is irritated.
- you are highly sensitive to sunlight.
- you are allergic to any of the ingredients in RENOVA (tretinoin cream) 0.02%. The active ingredient is tretinoin. Ask your doctor or pharmacist about the inactive ingredients.

RENOVA (tretinoin cream) 0.02% can cause increased skin irritation and increased chance of sunburn.

Tell your doctor if you have any skin condition. RENOVA (tretinoin cream) 0.02% may not be right for you.

Because RENOVA (tretinoin cream) 0.02% may make your skin more likely to burn from sunlight, tell your doctor if you are using other medicines that increase sensitivity to sunlight. You should not use RENOVA (tretinoin cream) 0.02% with such medicines. These include, but are not limited to:

- thiazides (to treat high blood pressure)
- tetracyclines, fluoroquinolones, sulfonamides (to treat infection)
- phenothiazines (to treat serious emotional problems)

If you are taking any prescription or non-prescription medicines, check with your doctor to make sure you can use RENOVA (tretinoin cream) 0.02% with them.

We do not know if RENOVA (tretinoin cream) 0.02% is passed to infants through breast milk. Therefore, tell your doctor if you are breast feeding.

How should I use RENOVA (tretinoin cream) 0.02%?

Use RENOVA (tretinoin cream) 0.02% as part of a total skin care and sun avoidance program. Follow your doctor’s instructions on how to use RENOVA (tretinoin cream) 0.02%. RENOVA (tretinoin cream) 0.02% is usually applied to the face once a day in the evening, following the three steps listed below:

1. Gently wash your face with a mild soap.
2. Pat the skin dry and wait 20 to 30 minutes before applying RENOVA (tretinoin cream) 0.02%.
3. TUBE: Squeeze a small amount of RENOVA (tretinoin cream) 0.02% (the size of a pearl—about 1/4 inch or 5 mm diameter) on your fingertip, and apply to your face.
PUMP: Fully depress the pump twice to dispense a small amount of RENOVA (tretinoin cream) 0.02% (the size of a pearl—about 1/4 inch or 5 mm diameter) on your fingertip, and apply to your face.

This should be enough to cover your affected area lightly.

Be especially careful when applying RENOVA (tretinoin cream) 0.02% to avoid your eyes, ears, nostrils, angles of the nose, and mouth. RENOVA (tretinoin cream) 0.02% may cause severe redness, itching, burning, stinging, and peeling if used on these areas.

Using too much RENOVA (tretinoin cream) 0.02% may increase discomfort and skin redness and peeling.

You may use cosmetics 1 hour after applying RENOVA (tretinoin cream) 0.02%. If you do, be sure to clean your face before applying RENOVA (tretinoin cream) 0.02% again. Skin moisturizers should be used at least every morning to protect the treated areas from dryness.

Use sunscreen and wear protective clothing to protect the treated areas from sunlight. If you sunburn easily, or if you spend a lot of time exposed to sunlight, be especially careful to protect your skin.

What should I avoid while using RENOVA (tretinoin cream) 0.02%?

RENOVA (tretinoin cream) 0.02% can make your treated skin more sensitive to sunlight. Therefore, keep out of the sunlight as much as possible and do not use sunlamps. Avoid as much as possible products that can increase skin irritation, such as:

- other skin medicines
- medicated or abrasive (rough) soaps
- permanent wave solutions
- chemical hair removers or waxes
- electrolysis
- products with alcohol, spices, astringents, or lime
- cleaners, shampoos, or cosmetics with a strong drying effect
- other products that may irritate your skin

What are the possible side effects of RENOVA (tretinoin cream) 0.02%?

You may feel brief warmth or stinging on your skin after you use RENOVA (tretinoin cream) 0.02%. Most patients report peeling, dry skin, burning, stinging, itching, and redness. These are usually mild to moderate and occur early in treatment. Contact your doctor if the side effects are a problem.

General advice about prescription medicines

Medicines are sometimes prescribed for conditions that are not mentioned in patient information leaflets. Only use RENOVA (tretinoin cream) 0.02% to treat the condition that your doctor has prescribed it for. Do not give RENOVA (tretinoin cream) 0.02% to other people. It may harm them.

This leaflet summarizes the most important information about RENOVA (tretinoin cream) 0.02%. If you would like more information, talk with your doctor. You can ask your pharmacist or doctor for information about RENOVA (tretinoin cream) 0.02% that is written for health professionals.

Storage: Store at 25°C (77°F); excursions permitted to 15° to 30°C (59° to 86°F).

Distributed by: Bausch Health US, LLC, Bridgewater, NJ 08807 USA

Manufactured by: Bausch Health Companies Inc., Laval, Quebec H7L 4A8, Canada

RENOVA is a registered trademark of Bausch Health Companies Inc. or its affiliates.

© 2025 Bausch Health Companies Inc. or its affiliates

This Patient Information has been approved by the U.S. Food and Drug Administration.

Rev. 11/2025 9418704

Package/Label Display Panel

NDC0187-5150-40
Rx only
RENOVA®
(tretinoin) Cream
0.02%
TUBE
For Topical Use Only
Net Wt. 40 g
Ortho Dermatologics